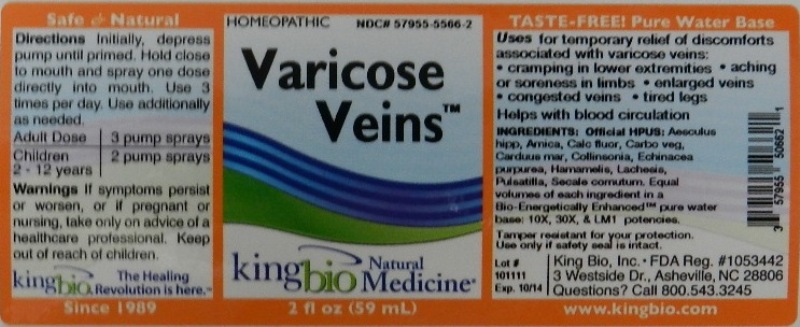 DRUG LABEL: Varicose Veins
NDC: 57955-5566 | Form: LIQUID
Manufacturer: King Bio Inc.
Category: homeopathic | Type: HUMAN OTC DRUG LABEL
Date: 20120103

ACTIVE INGREDIENTS: HORSE CHESTNUT 10 [hp_X]/59 mL; ARNICA MONTANA 10 [hp_X]/59 mL; CALCIUM FLUORIDE 10 [hp_X]/59 mL; ACTIVATED CHARCOAL 10 [hp_X]/59 mL; SILYBUM MARIANUM SEED 10 [hp_X]/59 mL; COLLINSONIA CANADENSIS ROOT 10 [hp_X]/59 mL; ECHINACEA PURPUREA 10 [hp_X]/59 mL; HAMAMELIS VIRGINIANA ROOT BARK/STEM BARK 10 [hp_X]/59 mL; LACHESIS MUTA VENOM 10 [hp_X]/59 mL; PULSATILLA VULGARIS 10 [hp_X]/59 mL; CLAVICEPS PURPUREA SCLEROTIUM 10 [hp_X]/59 mL
INACTIVE INGREDIENTS: WATER

Varicose Veins

Active Ingredients

Official HPUS: Aesculus hippocastanum,Arnica montana, Calcarea fluorica, Carbo vegetabilis, Carduus marianus, Collinsonia canadensis, Echinacea purpurea. Hamamelis virginiana, Lachesis mutus, Pulsatilla and Secale cornutum.

Reference image varicose veins.jpg

Inactive Ingredient

Equal volumes of each ingredient in a Bio-Energetically Enhanced, pure water base: 10X, 30X and LM1 potencies.

Reference image varicose veins.jpg

Dosage and Administration

Directions: Initially, depress pump until primed. Hold close to mouth and spray one dose directly into mouth. Use 3 times per day. Use additionally as needed.

Adult Dose 3 pump sprays

Children 2 - 12 years 2 pump sprays

Reference image varicose veins.jpg

Purpose

Uses for temporary relief of discomforts associated with varicose veins:

- cramping in lower extremities
- aching or soreness in limbs
- enlarged veins
- congested veins
- tired legs

Helps with blood circulation.
Reference image varicose veins.jpg

Warnings

If Symptoms persist or worsen, or if pregnant or nursing, take only on advice of a healthcare professional.

Tamper resistant for your protection. Use only if safety seal is intact.

Reference image varicose veins.jpg

Keep out of reach of children.

Reference image varicose veins.jpg

Indications and Usage

Uses for temporary relief of discomforts associated with varicose veins: cramping in lower extremities, aching or soreness in limbs, enlarged veins, congested veins, tired legs.

Helps with blood circulation.
Reference image varicose veins.jpg

PACKAGE LABEL

King Bio Inc.

3 Westside Drive

Asheville, NC 28806

Questions? Call 800.543.3245

www.kingbio.com

Safe and Natural Homeopathic spray